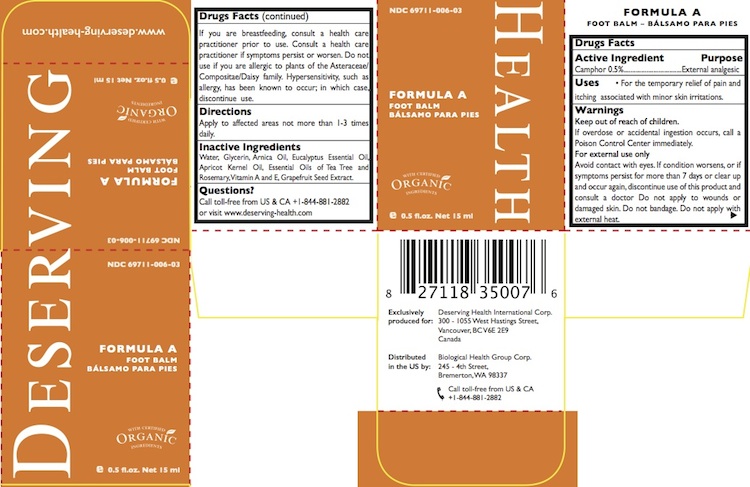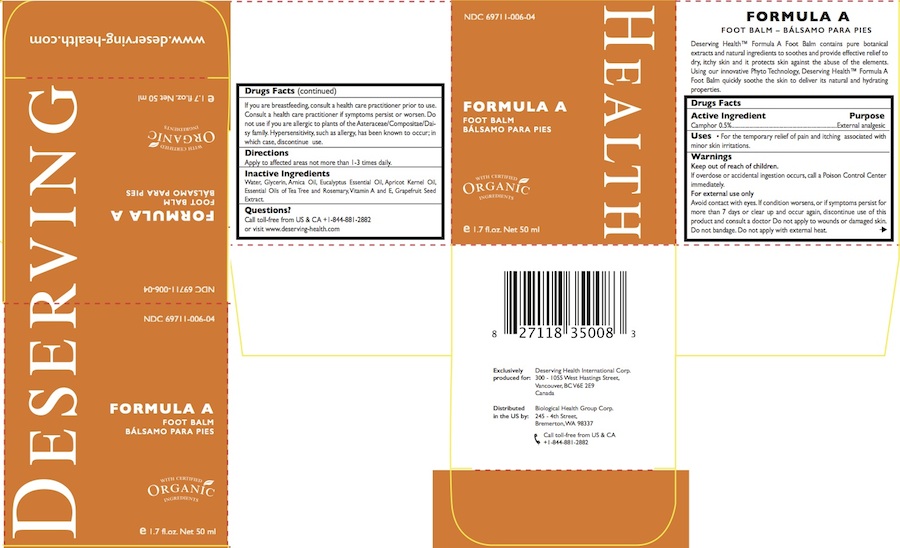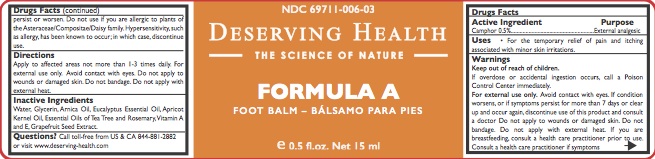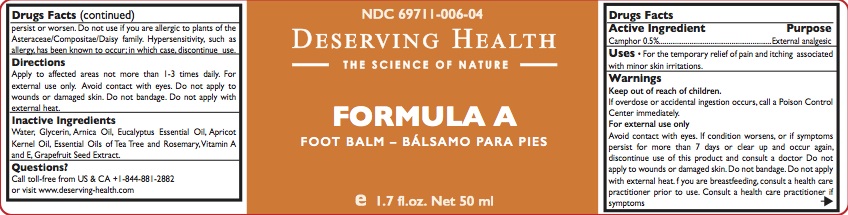 DRUG LABEL: FORMULA A
NDC: 69711-006 | Form: CREAM
Manufacturer: Biological Health Group Corporation
Category: otc | Type: HUMAN OTC DRUG LABEL
Date: 20150618

ACTIVE INGREDIENTS: CAMPHOR (NATURAL) 0.5 g/100 mL
INACTIVE INGREDIENTS: CITRUS PARADISI SEED; WATER; GLYCERIN; ARNICA MONTANA; EUCALYPTUS GUM; .ALPHA.-TOCOPHEROL; APRICOT KERNEL OIL; TEA TREE OIL; ROSEMARY OIL; VITAMIN A

FORMULA A
FOOT BALM - BÁLSAMO PARA PIES

Active ingredients Purpose

Camphor – 0.5% External Analgesic

Purpose

External analgesic

Uses

• For the temporary relief of pain and itching associated with minor skin irritations.

Warnings

For external use only.
Avoid contact with eyes.

PREGNANCY OR BREAST FEEDING

If you are breastfeeding, consult a health care practitioner prior to use.

Stop use and ask a doctor if

• if condition worsens, or if symptoms persist for more than 7 days or clear up and occur again, discontinue use of this product and consult a doctor .

KEEP OUT OF REACH OF CHILDREN

Keep out of reach of the children. If overdose or accidental ingestion occurs, call a Poison Control Center immediately.

Directions

Apply to affected areas not more than 1-3 times daily.

Inactive ingredients

Water, Glycerin, Arnica Oil, Eucalyptus Essential Oil, Apricot Kernel Oil, Essential Oils of Tea Tree and Rosemary,Vitamin A and E, Grapefruit Seed Extract.

Questions?

Call toll-free from US & CA +1-844-881-2882 or visit www.deserving-health.com

Do not use if you are allergic to plants of the Asteraceae/Compositae/Daisy family. Hypersensitivity, such as allergy, has been known to occur; in which case, discontinue use.
Consult a health care practitioner if symptoms persist or worsen.